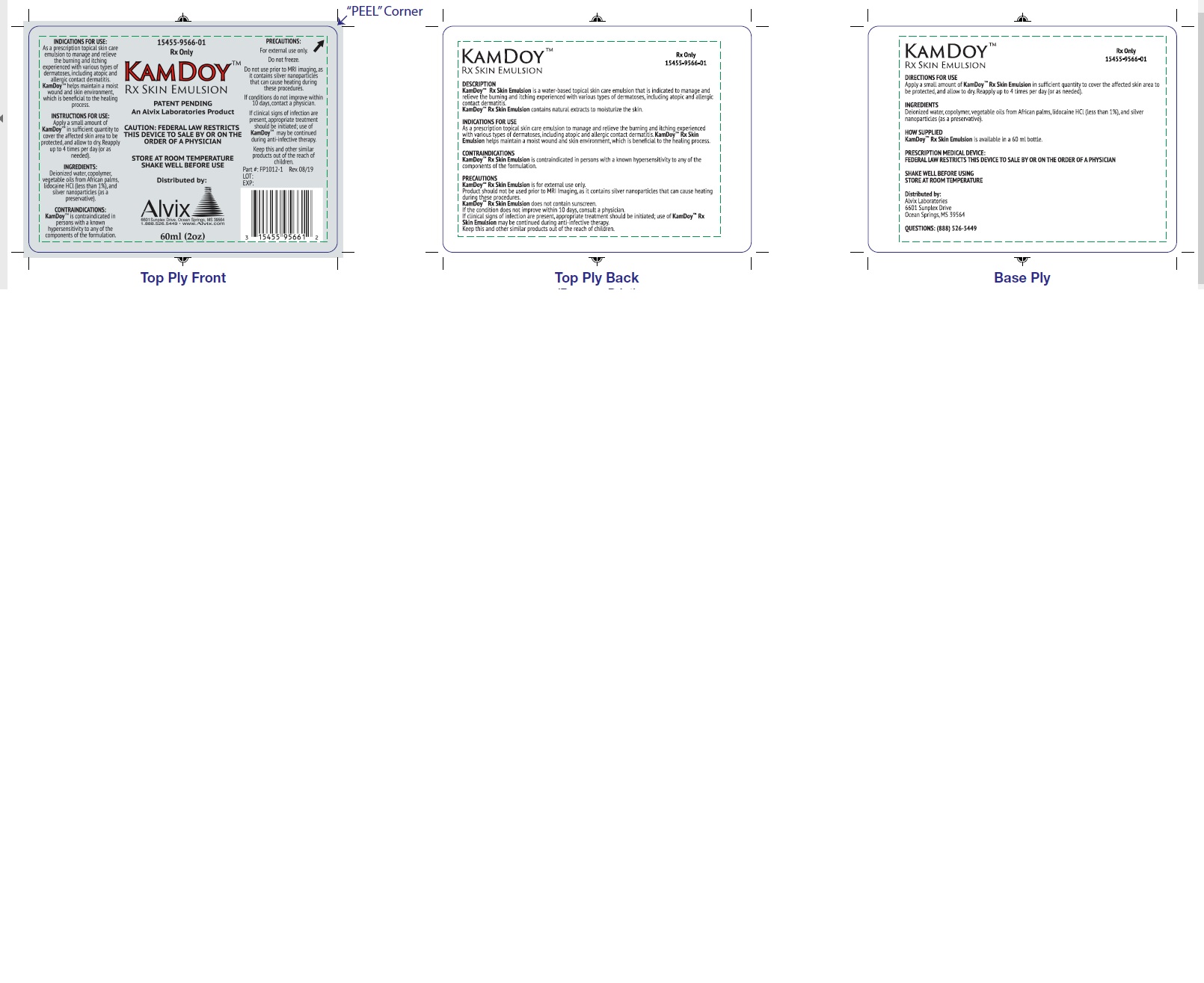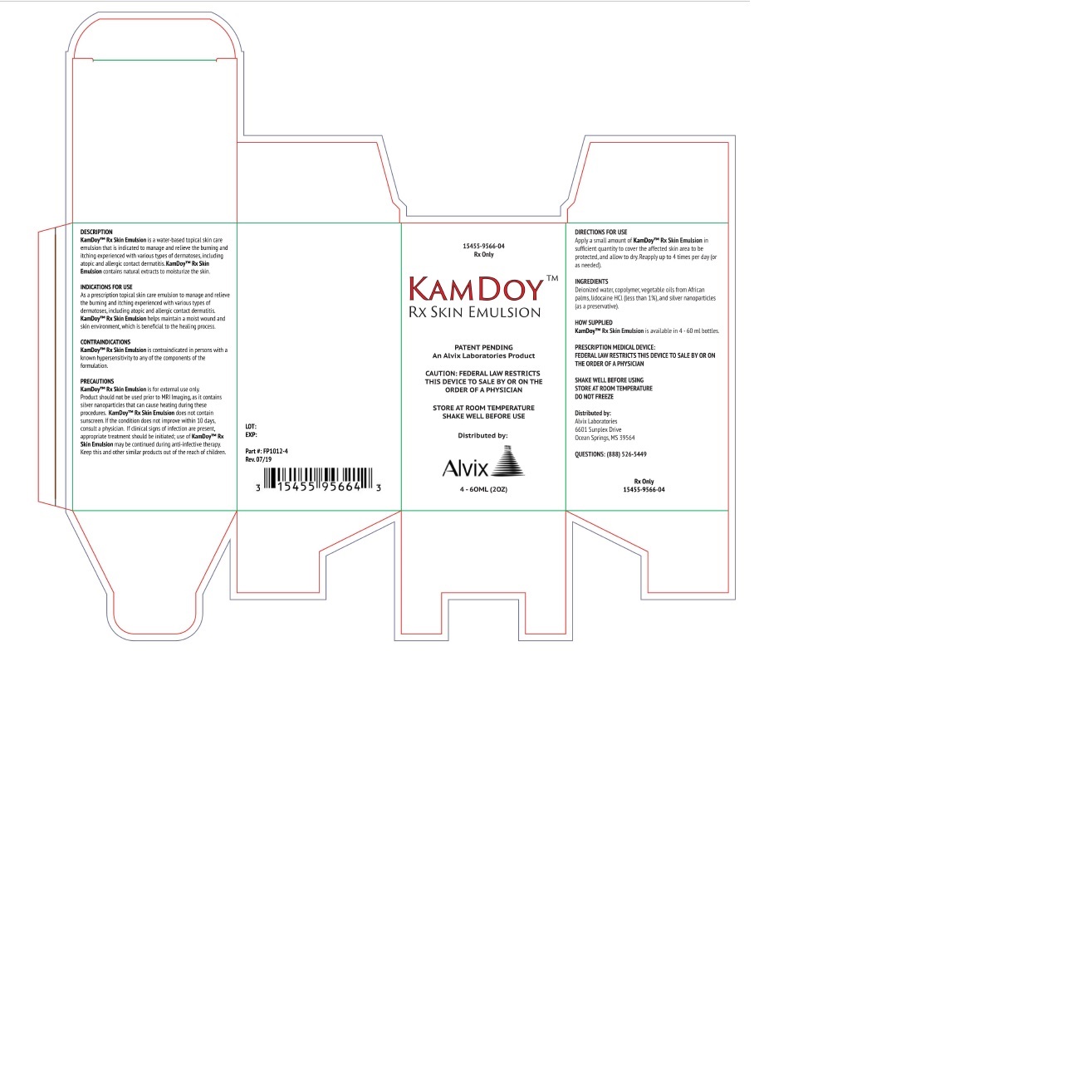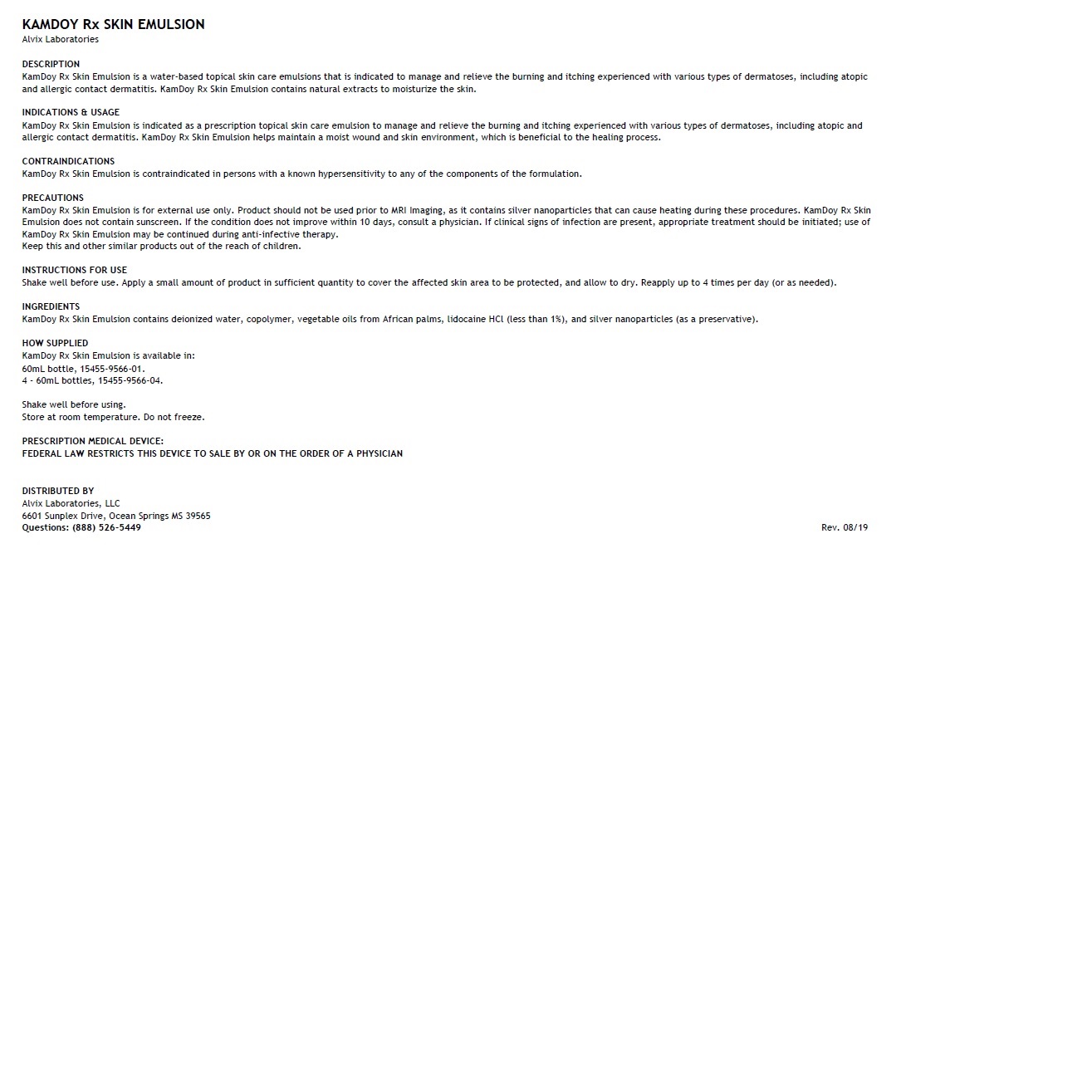 DRUG LABEL: KamDoy Skin Emulsion
NDC: 15455-9566
Manufacturer: Alvix Laboratories
Category: other | Type: PRESCRIPTION MEDICAL DEVICE LABEL
Date: 20190912

KamDoy Rx Skin Emulsion

DESCRIPTION

KamDoy Rx Skin Emulsion is a water-based topical skin care emulsions that is indicated to manage and relieve the burning and itching experienced with various types of dermatoses, including atopic and allergic contact dermatitis. KamDoy Rx Skin Emulsion contains natural extracts to moisturize the skin.

INDICATIONS & USAGE

KamDoy Rx Skin Emulsion is indicated as a prescription topical skin care emulsion to manage and relieve the burning and itching experienced with various types of dermatoses, including atopic and allergic contact dermatitis. KamDoy Rx Skin Emulsion helps maintain a moist wound and skin environment, which is beneficial to the healing process.

CONTRAINDICATIONS

KamDoy Rx Skin Emulsion is contraindicated in persons with a known hypersensitivity to any of the components of the formulation.

PRECAUTIONS

KamDoy Rx Skin Emulsion is for external use only. Product should not be used prior to MRI Imaging, as it contains silver nanoparticles that can cause heating during these procedures. KamDoy Rx Skin Emulsion does not contain sunscreen. If the condition does not improve within 10 days, consult a physician. If clinical signs of infection are present, appropriate treatment should be initiated; use of KamDoy Rx Skin Emulsion may be continued during anti-infective therapy.
Keep this and other similar products out of the reach of children.

INGREDIENTS

KamDoy Rx Skin Emulsion contains deionized water, copolymer, vegetable oils from African palms, lidocaine HCl (less than 1%), and silver nanoparticles (as a preservative).

HOW SUPPLIED

KamDoy Rx Skin Emulsion is available in:
60mL bottle, 15455-9566-01.
4 - 60mL bottles, 15455-9566-04.

Shake well before using.
Store at room temperature. Do not freeze.

PRESCRIPTION MEDICAL DEVICE:
FEDERAL LAW RESTRICTS THIS DEVICE TO SALE BY OR ON THE ORDER OF A PHYSICIAN

DISTRIBUTED BY
Alvix Laboratories, LLC
6601 Sunplex Drive, Ocean Springs MS 39565
Questions: (888) 526-5449